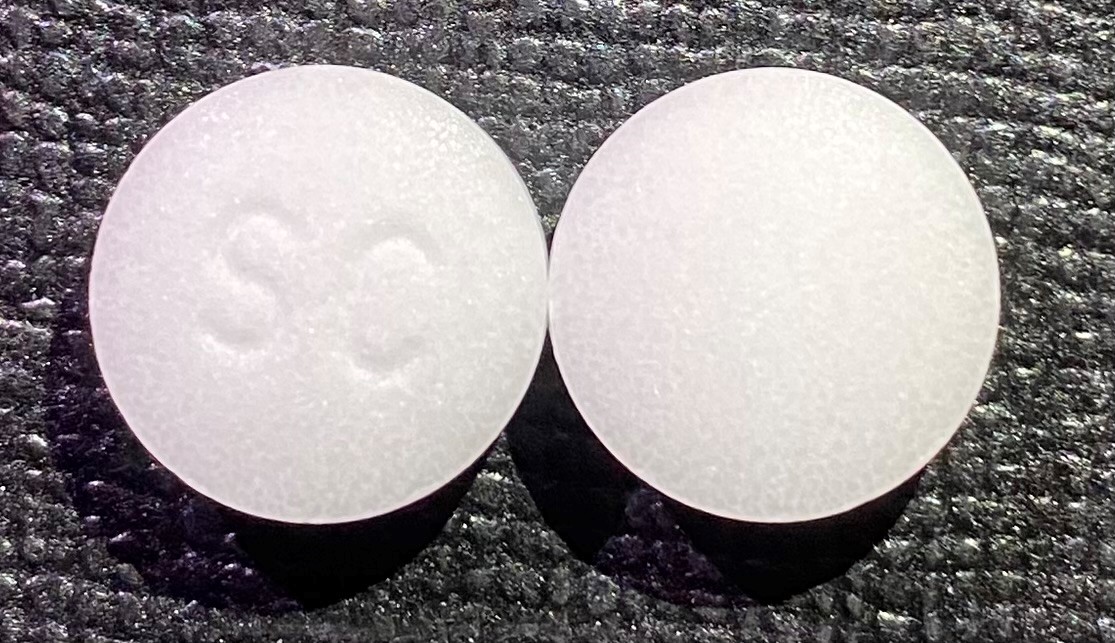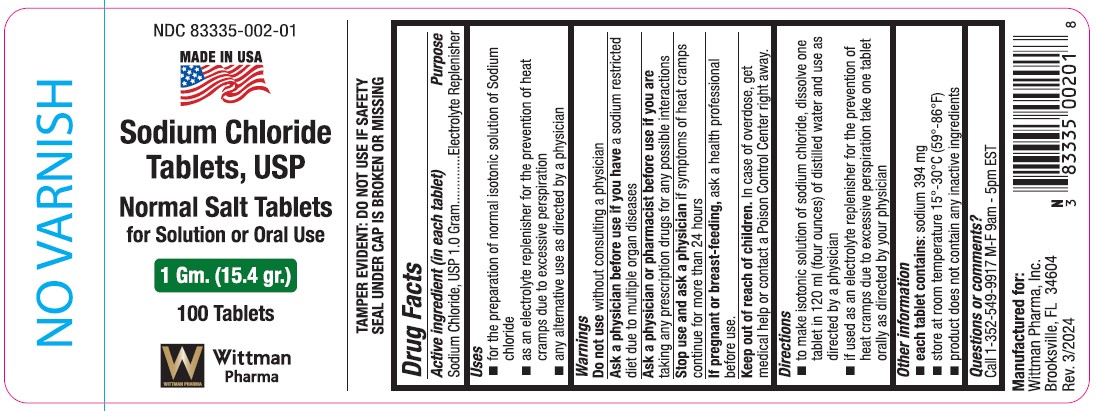 DRUG LABEL: Sodium Chloride
NDC: 83335-002 | Form: TABLET
Manufacturer: Wittman Pharma, Inc.
Category: otc | Type: HUMAN OTC DRUG LABEL
Date: 20240404

ACTIVE INGREDIENTS: SODIUM CHLORIDE 1 g/1 g

Sodium Chloride Tablets

Directions

- to make isontonic solution of sodium chloride, dissolve one tablet in 120 ml (four ounces) of distilled water and use as directed by a physician.

- if used as an electrolyte replenisher for the prevention of heat cramps due to excessive perspiration take one tablet orally as directed by your physician.

Warnings

Do not use without consulting a physician

Ask a physician before use if you have a sodium restricted diet due to multiple organ diseases

Stop use and ask a physician if symptoms of heat cramps continue for more than 24 hours.

If pregnant or breast-feeding, ask a health professional before use.

Keep out of reach of children.

In case of overdose, get medical help or contact a Poison Control Center right away.

INACTIVE INGREDIENT

None

Uses

- for the preparation of normal isotonic solution of sodium chloride

- as an electrolyte replenisher for the prevention of heat cramps due to excessive perspiration

- any alternative use as directed by a physician

Keep out of reach of children.

Purpose

Electrolyte Replenisher

Active ingredient (in each tablet)

Sodium Chloride, USP 1.0 gram

Drug Facts

Active ingredient (in each tablet)

Sodium Chloride, USP 1.0 gram

Purpose

Electrolyte Replenisher

Uses

- for the preparation of normal isotonic solution of sodium chloride

- as an electrolyte replenisher for the prevention of heat cramps due to excessive perspiration

- any alternative use as directed by a physician

Warnings

Do not use without consulting a physician

Ask a physician before use if you have a sodium restricted diet due to multiple organ diseases

Stop use and ask a physician if symptoms of heat cramps continue for more than 24 hours.

If pregnant or breast-feeding, ask a health professional before use.

Keep out of reach of children.

In case of overdose, get medical help or contact a Poison Control Center right away.

Directions

- to make isontonic solution of sodium chloride, dissolve one tablet in 120 ml (four ounces) of distilled water and use as directed by a physician.

- if used as an electrolyte replenisher for the prevention of heat cramps due to excessive perspiration take one tablet orally as directed by your physician.

Other information

- each tablet contains: sodium 394 mg

- store at room temperature 15°-30°C (59°-86°F)

- product does not contain any inactive ingredients

Questions or comments?

Call 1-352-549-9917 M-F 9am - 5pm EST